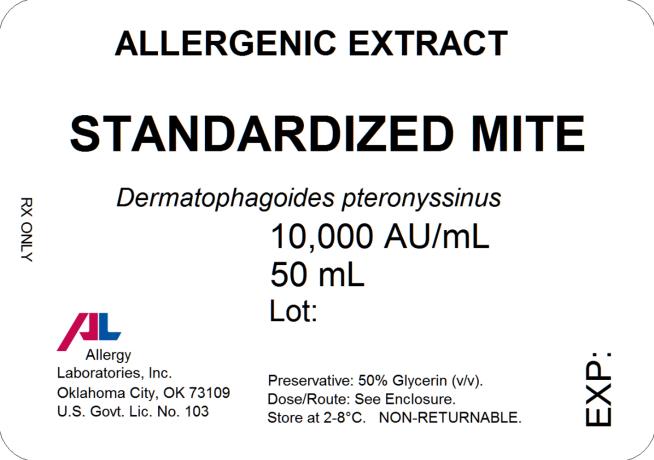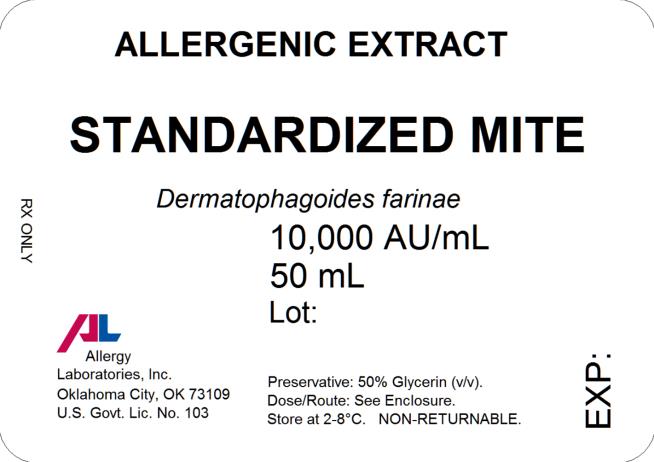 DRUG LABEL: STANDARDIZED MITE D FARINAE
NDC: 54575-325 | Form: INJECTION, SOLUTION
Manufacturer: Allergy Laboratories, Inc.
Category: other | Type: STANDARDIZED ALLERGENIC
Date: 20170810

ACTIVE INGREDIENTS: DERMATOPHAGOIDES FARINAE 10000 [AU]/1 mL
INACTIVE INGREDIENTS: GLYCERIN 0.5 mL/1 mL; SODIUM CHLORIDE 0.00166 g/1 mL; SODIUM BICARBONATE 0.0091 g/1 mL; WATER

Standardized Mites

Oklahoma City, OK 73109

INSTRUCTIONS AND DOSAGE SCHEDULE FOR
STANDARDIZED ALLERGENIC
EXTRACTS MITE EXTRACT

(Dermatophagoides farinae) (Dermatophagoides pteronyssinus)

WARNING

This product is intended for use by physicians who are experienced in the administration of allergenic extracts and the emergency care of anaphylaxis, or for use under the guidance of an allergy specialist.

Extracts standardized using the Allergy Unit may be more potent than extracts based on the weight to volume or PNU methods of expressing potency. Allergy Laboratories extract is not directly interchangeable with other allergenic extracts. The initial dose must be based on skin testing as described in the dosage and administration section of this insert. Patients being switched from other types of extracts to Allergy Laboratories should be started as though they were coming under treatment for the first time. Patients should be instructed to recognize adverse reaction symptoms and cautioned to contact physicians office if reaction symptoms occur. As with all allergenic extracts, severe systemic reactions may occur. In certain individuals these life threatening reactions may be fatal. Patients should be observed for at least 30 minutes following treatment and emergency measures as well as personnel trained in their use should be immediately available in the event of a life threatening reaction.

This product should not be injected intravenously. Subcutaneous injections are recommended.

Patients who are taking non-selective beta blockers may be more reactive to allergens given for testing or treatment and may be unresponsive to the usual doses of epinephrine used to treat allergic reactions.

Refer also to the warnings, precautions, adverse reactions and dosage sections below.

DESCRIPTION

The standardized mite extract contains the extractables of Dermatophagoides farinae or Dermatophagoides pteronyssinus. The standardized (Allergy Unit) extract in these vials is designed primarily for the physician equipped to prepare dilutions and mixtures as required. The extract is sterile and contains 50% (v/v) glycerine as a preservative. It is intended for subcutaneous injection. Source material for the mite extract is the whole bodies of the mite. The mites are grown on a medium containing yeast and pork and are processed in a manner to remove at least 99% of the growth medium. The medium contains no material of human origin. Several manufacturers submitted intradermal skin test data on an extract of mite medium from one supplier using patients who were puncture test reactive (∑ E ≥40mm) to mite extracts. By intradermal testing there was one reaction (∑ E ≥20mm) in 44 individuals at an estimated 1% level of medium content of mites, and 4 reactions in 40 individuals at an estimated 10% content. Two of the individuals who were skin test reactive to the mite extract and who were also skin test reactive to the mite medium extract were also skin tested by puncture method with an extract of yeast (Saccharomyces sp.) and were reactive.

The mite extract is standardized by assay using ELISA Competition (1) against a reference extract distributed by the Center for Biologics Evaluation and Research, U.S. Food and Drug Administration. Potency based on Allergy Units (AU/ml) is printed on the label. The F.D.A. reference extract has been assigned 10,000 AU/ml based on quantitative skin testing (2). The mite extract is labeled 10,000 AU/ml because it is statistically equivalent in potency to the reference extract.

INACTIVE INGREDIENTS

Glycerinated extracts contain:
glycerine | 50.0 % v/v
sodium chloride | 0.166 % w/v
sodium bicarbonate | 0.091 % w/v

CLINICAL PHARMACOLOGY

The allergic state is initiated by an immune response inducing B cells to produce IgE antibodies to specific allergens. IgE antibodies bind to surface receptors on mast cells and basophils.

When antigens gain access to the immune system they react with the bound IgE. The reacting antigen to the surface bound IgE stimulates a number of chemical mediators to be released from the mast cells and basophils. These include histamine, Eosinophil Chemotactic Factor (ECF-A) and leukotrienes. These chemical mediators are pharmacologically active at low concentrations and are partially responsible for the biological manifestation of the allergic response. (3)

The mechanism by which immunotherapy achieves hyposensitization is not completely understood. There is an increase in “blocking antibody” (IgG) titer and in some patients a decrease in specific IgE, a decrease in histamine release to specific allergen and an increase in suppressor cell population to specific allergen. These changes may occur only after prolonged therapy. (4)

INDICATIONS AND USAGE

Standardized mite extract is used for the diagnosis and treatment of allergic disease to mite. Diagnosis of allergic disease to mite is made through a combined medical history sufficiently complete to identify allergic symptoms to mite and identification of mite allergy by diagnostic skin testing.

Hyposensitization therapy to mite is treatment for patients exhibiting allergic reactions to mite. Immunotherapy is intended for patients whose symptoms cannot be satisfactorily controlled by avoidance of the offending allergen or by the use of symptomatic medications. (5)

CONTRAINDICATIONS

There are no known absolute contraindications to hyposensitization therapy. See precautions section for pregnancy risks.

A patient should not be treated with allergens unless a history of symptoms and a positive skin test reaction have been demonstrated. Allergenic extracts should only be administered to patients that show symptoms of allergy or asthma. The physician must determine if the benefits outweigh the risks in using these products for treating these patients.

Patients who are taking non-selective beta blockers may be more reactive to allergens given for testing or treatment and may be unresponsive to the usual doses of epinephrine used to treat allergic reactions.

WARNINGS See WARNINGS at the beginning of the instruction sheet.
Extracts standardized using the Allergy Unit may be more potent than extracts based on weight to volume or PNU methods of expressing potency. Comparative skin tests can be performed to determine the relative potency before initial use of new extracts. DO NOT GIVE ALLERGY INJECTIONS INTRAVENOUSLY. Subcutaneous injections are recommended. Injections may produce large local reactions that may be painful to the patient. DO NOT GIVE FULL STRENGTH INJECTIONS UNTIL THE COMPARATIVE STRENGTH IS DETERMINED. After inserting the needle, but before injecting extract, withdraw the plunger slightly. If blood appears in the syringe, re-insert the needle at another site. Careful selection of dose and injection should prevent most systemic reactions.

PRECAUTIONS

(1) GENERAL:

The dosage should be reduced 50-75% from the previous dose when starting a patient on a new lot of standardized mite extract from the same manufacturer or from a different manufacturer. When changing from a non-standardized mite extract to a standardized mite extract the dose should be based upon comparative skin testing or the patient should be treated as though beginning treatment for the first time.

A separate sterile tuberculin type syringe should be used with each patient to prevent cross contamination of extracts. This will also prevent transmission of disease such as serum hepatitis, AIDS and other infectious diseases. Aseptic technique should always be used when injections of allergenic extracts are administered.

(2) INFORMATION FOR PATIENTS:

Because most serious reactions following the administration of allergenic extracts occur within 20 minutes of the injection, the patient should remain under observation for this period of time. The size of the local reaction should be recorded, because increasingly large local reaction may precede a subsequent systemic reaction with increasing dosage. The patient should be instructed to report any unusual reactions to the attention of the physician. In particular, this includes swelling and/or tenderness at the injection site or reactions such as rhinorrhea, sneezing, coughing, wheezing, shortness of breath, nausea, dizziness or faintness.

(3) DRUG INTERACTIONS:

Patients who are taking non-selective beta blockers may be more reactive to allergens given for testing or treatment and may be unresponsive to the usual doses of epinephrine used to treat allergic reactions. Antihistamines can significantly inhibit the immediate skin test reactions. Patients should be free of such medication for at least 48 hours before testing.

(4) CARCINOGENESIS, MUTAGENESIS, IMPAIRMENT OF FERTILITY:

Long term studies with extracts have not been conducted in animals to determine their potential for carcinogenesis, mutagenesis, or impairment of fertility.

(5) PREGNANCY: Pregnancy Category C.

Animal reproduction studies have not been conducted with allergenic extracts.

It is also not known whether allergenic extracts can cause fetal harm when administered to a pregnant woman or can affect reproduction capacity. Allergenic extracts should be given to a pregnant woman only if clearly needed.

Controlled studies of hyposensitization with moderate to high doses of allergenic extracts in pregnant women have failed to demonstrate any risk to the mother or fetus. (6)

However, with histamines known ability to contract uterine muscles any reaction which would release significant amounts of histamine such as hyposensitization overdose should be avoided. The physician must weigh the benefits of immunotherapy against the risk of anaphylactic reactions that could result in harm to the mother and/or fetus.

Hyposensitization should be used during pregnancy only if clearly necessary and administered cautiously. If a woman is on maintenance dose, the occurrence of pregnancy is not an indication to stop injection therapy.

(6) NURSING MOTHERS:

It is not known if allergenic extracts are excreted in human milk therefore caution should be exercised when extracts are administered in nursing women.

(7) PEDIATRIC USE:

Standardized mite extract has not been studied in children, so the safety in children has not been established. Doses of allergenic extracts for children are generally the same as those for adults. The extracts may cause some pain or discomfort when injected. The maximum tolerated dose may be less than the adult dose due to the smaller size of the child. Therefore the volume of the dose may need to be adjusted from the adult schedules provided.

ADVERSE REACTIONS

(1). Local Reactions:

Some swelling and redness at the site of injection is not unusual. Mild burning that occurs immediately after the injection is normal; this usually subsides in 10 to 20 seconds. If the swelling and redness persist for a period of 24 hours or longer this should be a sign to proceed with caution in increasing the dosage. With the next injection the dosage should remain the same or be decreased. Large local reactions may indicate that a systemic reaction could occur with the next injection if the dosage was increased. If a patient continues to have reactions at the maintenance dose, the patient is considered to have exceeded the maximum tolerated dosage.

(2). Systemic Reactions:

Systemic reactions occur infrequently but must be looked for in all patients, especially highly sensitive patients. Anaphylactic shock and death are always possible, therefore, physicians must be prepared for the treatment of these reactions. Systemic reactions can also be characterized by one or more of the following symptoms: angioedema, tachycardia, conjunctivitis, cough, fainting, hypotension, pallor, rhinitis, urticaria and wheezing.

Systemic reaction can be treated by the immediate application of a tourniquet above the site of injection and the administration of 0.3 to 0.5ml of 1:1000 Epinephrine-Hydrochloride subcutaneously or intramuscularly at the site of allergen injection. The dosage may be repeated two times at 15 minute intervals. Loosen the tourniquet at least every 10 minutes.

The pediatric dosage for 1:1000 Epinephrine-Hydrochloride is 0.05 to 0.1ml for infants to 2 years of age; 0.15ml for children 2 to 6 years; and 0.2ml for children 6 to 12 years.

Patients should always be observed for at least 30 minutes after any injection. Hypotension can be reversed by using vasopressor agents and volume expanders. Parenteral aminophylline and inhalation bronchodilators may be required for bronchospasm. Oxygen may also be needed. Maintenance of an open airway is critical if upper airway obstruction is present. Adrenal corticosteroids and intravenous antihistamine can be given after adequate epinephrine and circulatory support has been administered. Physicians must be familiar with these systemic reactions and have all the equipment and drugs necessary for proper treatment. (7)

DOSAGE AND ADMINISTRATION

DIAGNOSTIC SKIN TESTING:

Puncture tests performed on 15 highly sensitive patients with 2 separate lots of 10,000 AU/ml Mite Extract (D. farinae) showed a mean sum of diameter wheal of 15.93mm ± 4.92 and a mean sum of diameter erythema of 63.70mm ± 16.46. Puncture tests performed on 10 highly sensitive patients with 10,000 AU/ml Mite Extract (D. pteronyssinus) showed a mean sum of diameter wheal of 17.00mm ± 3.39 and a mean sum of diameter erythema of 84.80mm ± 5.80.

Intradermal skin test results in highly sensitive patients is shown below using the same lots as used in the puncture tests above.

 |  | AU/ml to elicit 50mm sum of Diameter of Erythema Reaction
Extracts | Number of Patients | Mean | Range
D. farinae | 15 | 1.328 | 0.0024-9.410
D. pteronyssinus | 10 | 0.008 | 0.0009-0.0287

Puncture tests with the mite growth medium as control were negative in 15 patients sensitive to mite.

These products are used to determine a patient’s sensitivity to specific antigens and aid in the diagnosis and treatment of atopic diseases. After a thorough history a decision can be made as to which allergens will be appropriate to use for testing. The recommended procedure is to initially perform puncture tests, then follow with intradermal tests. See recommended dosage below.

SCRATCH OR PUNCTURE TEST:

Concentration AU/ml |  | Dosage ml
10,000 |  | 0.05

INTRADERMAL TEST:

A. Patients with a negative scratch or puncture test.

Concentration AU/ml

Dosage ml

1) 50 AU/ml or

0.02

2)100 AU/ml * if

0.02

50 AU/ml is

negative

B. Patients tested by intradermal only.

Concentration AU/ml

Dosage ml

0.05 AU/ml

0.02

If negative repeat

tests with stronger

concentrations until

a maximum of 100 AU/ml*

is reached

0.02

*The negative intradermal control used for the 100 AU/ml concentration should contain
0.05% (v/v) glycerine.

FREQUENCY OF ADMINISTRATION:

The number of skin tests applied at one time will depend on the particular patient and their allergic history. These tests should be performed and observed in 15 to 20 minutes. Additional tests may be applied in sequence. Perform tests on the anterolateral aspect of the upper arm on an area that permits the effective application of a tourniquet proximal to the site of the test. The skin at the site of injection should be disinfected with rubbing alcohol before testing.

Puncture testing: Apply one drop (0.05ml) of extract to the skin. Pierce the drop of extract and skin using a sterile hypodermic needle or vaccinating needle. Maintain the needle perpendicular to the skin surface and rock the needle back and forth to produce a small hole without bleeding. Do not rotate or gouge the needle. Remove needle from skin and wipe excess extract from skin surface.

Scratch testing: Using a scarifier or needle, make a scratch 1/16 inch long on the epidermis penetrating the outer cornified area but being careful not to draw blood. Apply one drop (0.05ml) of allergen to the scratch.

Intradermal testing: Use a separate sterile syringe (tuberculin type equipped with a 27 gauge by 3/8 inch needle with intradermal bevel) for each antigen. The tests are made by injecting 0.02ml of allergen into the epidermis. If the test has been performed properly, the solution should raise a bleb 2 to 3mm in diameter. If the bleb does not appear, the injection was made too deeply.

A negative control consisting of the same solution that the extract was prepared in should be applied to one of the sites in the same manner as the tests being performed. For example, the negative intradermal control should contain 0.5% (v/v) glycerine, if a 100 AU/ml concentration mite is used for intradermal testing. Histamine phosphate should be used as a positive control for evaluation of skin testing. Histamine phosphate is available from other manufacturers. See their directions for use, for recommended dosage and interpretation of results.

A positive reaction usually develops in 15-20 minutes. The positive response is a wheal and flare reaction that is larger than the negative control and judged on the size of the reaction. Scratch or puncture tests may not elicit as large and well defined reaction as the intradermal. (5)

The following system is recommended (8):

Reaction |  |  | Erythema |  |  | Wheal
0 |  |  | < 5mm |  |  | < 5mm
+ |  |  | 5-10mm |  |  | 5-10mm
1+ |  |  | 11-20mm |  |  | 5-10mm
2+ |  |  | 21-30mm |  |  | 5-10mm
3+ |  |  | 31-40mm |  | 10-15mm or with pseudopods >15mm or with many pseudopods
4+ |  |  | >40mm

IMMUNOTHERAPY:

The following are two methods of injection therapy:

1. Pre-seasonal in which treatment is begun three months before seasonal difficulty begins and brought to maintenance dose by injections 4 to 7 days apart and discontinued after that season ends.

2. Perennial treatment is the recommended mode of therapy in which the patient is, by injection therapy, brought up to tolerated maintenance dose and remains at that dose until amelioration of allergic symptoms occurs. Injections may be given at intervals of 4 to 7 days.

Allergenic extracts must be diluted before use. Normally immunotherapy can be started with a 1 AU/ml dilution. If a patient appears to be extremely sensitive, dilutions of the antigen can further be made before injections are started. The following are suggested procedures for making a proper dilution series. Recommended diluents contain 0.9% sodium chloride and 0.4% phenol as a preservative. Allergenic extracts should be inspected visually for particulate matter and discoloration prior to administration, whenever solution and container permit.

TEN FOLD DILUTION SERIES
Extract Volume | Extract Concentration AU/mL | Diluent Volume | Dilution Concentration AU/mL
1 part | 10,000 + | 9 parts= | 1,000
1 part | 1,000 + | 9 parts= | 100
1 part | 100 + | 9 parts= | 10
1 part | 10+ | 9 parts= | 1

Perennial treatment may be started using the following dosage and dilution schedule. THIS SCHEDULE IS ONLY ILLUSTRATIVE AND HAS NOT BEEN SUBJECTED TO ADEQUATE OR WELL-CONTROLLED TRIALS TO DETERMINE EITHER ITS SAFETY OR EFFICACY.

dose # | Dose volume | Concentration
1 | 0.05 | 1 AU/ml
2 | 0.10
3 | 0.20
4 | 0.30
5 | 0.40
6 | 0.50
7 | 0.05 | 10 AU/ml
8 | 0.10
9 | 0.20
10 | 0.30
11 | 0.40
12 | 0.50
13 | 0.05 | 100 AU/ml
14 | 0.10
15 | 0.20
16 | 0.30
17 | 0.40
18 | 0.50
19 | 0.05 | 1,000 AU/ml
20 | 0.10
21 | 0.20
22 | 0.30
23 | 0.40
24 | 0.50
25 | 0.05 | 10,000 AU/ml
26 | 0.10
27 | 0.20
28 | 0.30
29 | 0.40
30 | 0.50

Gradually increase the dose as outlined in the schedule. If you give a dose that causes a mild local reaction manifested by warmth or redness, repeat the same dose. If the reaction is severe or systemic (manifested as hives, asthma, or hay fever), drop back a dose in schedule and build again. If a severe local reaction or a systemic reaction is again encountered, this should be considered more than the maximum tolerance for this patient. The maintenance dose is the largest dose that relieves symptoms without producing local reactions. The size and interval of doses will vary and can be adjusted as necessary. The normal interval between doses is 4 to 7 days.

HOW SUPPLIED

Bulk extract (stock concentrate) in 50% (v/v) glycerine containing 10,000 AU/ml is supplied in 10ml, 30ml, and 50ml vials. Scratch testing in 50% (v/v) glycerine containing 10,000 AU/ml is supplied in 2ml dropper vials. Intradermal testing (aqueous) containing 100 AU/ml is supplied in 5ml vials.

STORAGE

These extracts should be stored at 2 to 8 degrees Celsius. Excessive heating (above room temperature) and repeated freeze-thawing should be avoided. The dating period (expiration date) is shown on the vial label. Once extracts are diluted the shelf life decreases. Extracts should be re-ordered when out of date. Please allow a minimum of three (3) weeks for delivery due to the holding period for sterility testing.

Revised 06/23/16

L-050-01

REFERENCES

1. ELISA Competition Assay, October 1993, In Methods of the Allergenics Products Testing Laboratory, Food and Drug Administration.

2. Turkeltaub, P., Rastogi, S.C., Baer, H.: Assignment of Allergy Units to Reference Preparations using the ID50EAL method, May 1986, In Methods of the Laboratory of Allergenic Products, Division of Bacterial Products, Food and Drug Administration.

3. Wasserman, S.I.: Biochemical mediators of allergic reactions. In Patterson, R. (ed): Allergic diseases: diagnosis and management, p. 86. Philadelphia, J.B. Lippincott Co. 1985.

4. Grammer, L.C.: Principle of immunologic management of allergic diseases due to extrinsic antigens. In Patterson, R. (ed): Allergic diseases: diagnosis and management, p. 358. Philadelphia, J.B. Lippincott Co. 1985.

5. Booth, B.H.: Diagnosis of Immediate Hypersensitivity. In Patterson, R. (ed): Allergic diseases: diagnosis and management, p. 102. Philadelphia, J.B. Lippincott Co. 1985.

6. Metzger, W.J., et al.: The safety of immunotherapy during pregnancy. J. Allergy Clin. Immunol., 64 (4): 268-272, 1978.

7. Patterson, R. et al.: Immunotherapy. In Middleton, E. Jr., Reed, C.E. and Ellis, E.F. (ed): Allergy; Principles and Practice, (Vol. 2) p. 1119, St. Louis, The C.V. Mosby Co. 1983.

8. Norman, P.S.: In vivo methods of study of allergy: Skin and Mucosal tests, techniques and interpretation. In Middleton, E Jr., Reed, C.E. and Ellis, E.F. (ed): Allergy Principles and Practice, (Vol 1), p. 258. St. Louis, The C.V. Mosby Co. 1978.

ALLERGY LABORATORIES, INC.
Oklahoma City, OK 73109

U.S. License #103

(405) 235-1451 ∙ 800-654-3971

PRINCIPAL DISPLAY PANEL

ALLERGENIC EXTRACT
STANDARDIZED MITE
Dermatophagoides pteronyssinus
10,000 AU/mL
50 mL
Rx Only

PRINCIPAL DISPLAY PANEL

ALLERGENIC EXTRACT
STANDARDIZED MITE
Dermatophagoides farinae
10,000 AU/mL
50 mL
Rx Only